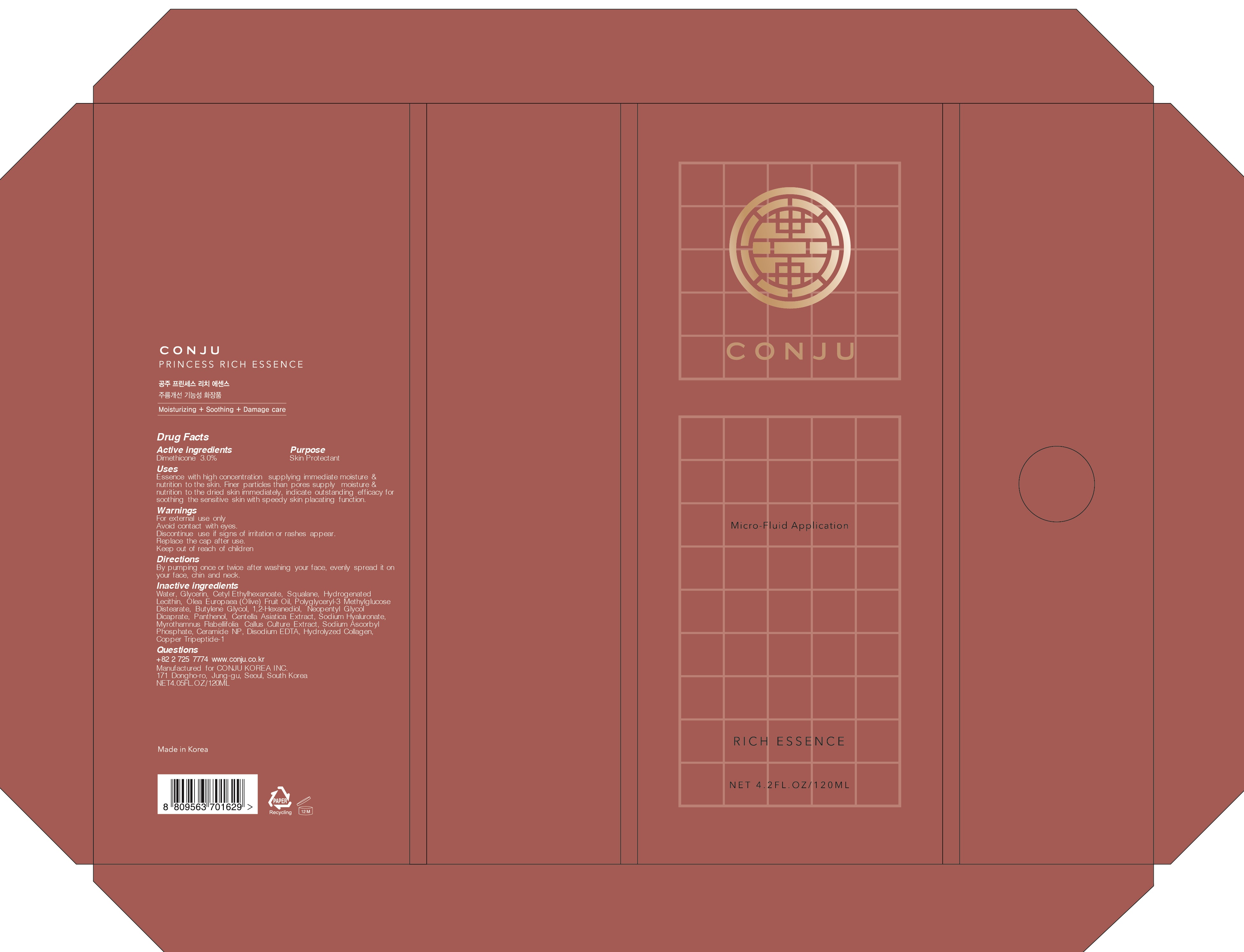 DRUG LABEL: CONJU PRINCESS RICH ESSENCE
NDC: 72950-010 | Form: LIQUID
Manufacturer: Conju Korea Inc.
Category: otc | Type: HUMAN OTC DRUG LABEL
Date: 20190318

ACTIVE INGREDIENTS: Dimethicone 3.6 g/120 mL
INACTIVE INGREDIENTS: Water; Glycerin

ACTIVE INGREDIENT

Active ingredient: Dimethicone 3.0%

INACTIVE INGREDIENT

Inactive ingredients:
Water, Glycerin, Cetyl Ethylhexanoate, Squalane, Hydrogenated Lecithin, Olea Europaea (Olive) Fruit Oil, Polyglyceryl-3 Methylglucose Distearate, Butylene Glycol, 1,2-Hexanediol, Neopentyl Glycol Dicaprate, Panthenol, Centella Asiatica Extract, Sodium Hyaluronate, Myrothamnus Flabellifolia Callus Culture Extract, Sodium Ascorbyl Phosphate, Ceramide NP, Disodium EDTA, Hydrolyzed Collagen, Copper Tripeptide-1

PURPOSE

Purpose: Skin Protectant

WARNINGS

For external use only
Avoid contact with eyes.
Discontinue use if signs of irritation or rashes appear.
Replace the cap after use.
Keep out of reach of children

KEEP OUT OF REACH OF CHILDREN

Uses

Essence with high concentration supplying immediate moisture & nutrition to the skin. Finer particles than pores supply moisture & nutrition to the dried skin immediately, indicate outstanding efficacy for soothing the sensitive skin with speedy skin placating function.

Directions

By pumping once or twice after washing your face, evenly spread it on your face, chin and neck.